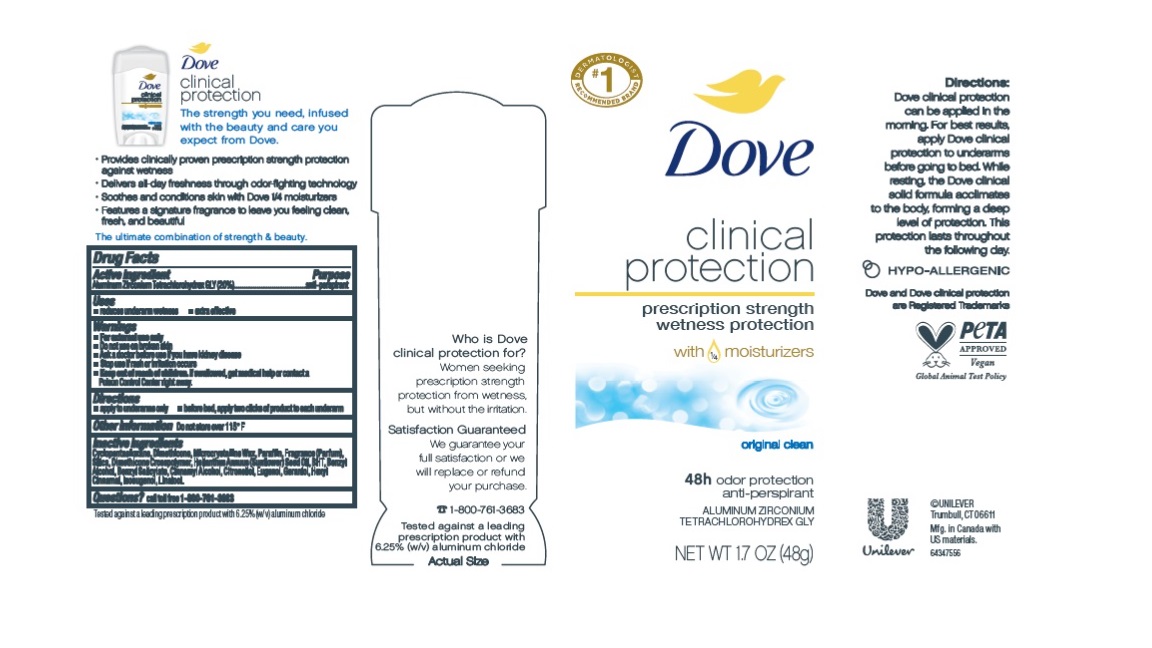 DRUG LABEL: Dove
NDC: 64942-2269 | Form: STICK
Manufacturer: Conopco Inc. d/b/a/ Unilever
Category: otc | Type: HUMAN OTC DRUG LABEL
Date: 20240408

ACTIVE INGREDIENTS: ALUMINUM ZIRCONIUM TETRACHLOROHYDREX GLY 20 g/100 g
INACTIVE INGREDIENTS: .BETA.-CITRONELLOL, (R)-; EUGENOL; MICROCRYSTALLINE WAX; PARAFFIN; SUNFLOWER OIL; CYCLOMETHICONE 5; BUTYLATED HYDROXYTOLUENE; SILICON DIOXIDE; DIMETHICONE; DIMETHICONE CROSSPOLYMER (450000 MPA.S AT 12% IN CYCLOPENTASILOXANE); CINNAMYL ALCOHOL; GERANIOL; BENZYL SALICYLATE; BENZYL ALCOHOL; .ALPHA.-HEXYLCINNAMALDEHYDE; LINALOOL, (+/-)-; ISOEUGENOL

Dove Clinical Protection Original Clean Antiperspirant & Deodorant

Drug Facts

Active ingredient

Aluminum Zirconium Tetrachlorohydrex GLY (20.0 %)

Purpose

antiperspirant

Uses

• reduces underarm wetness
• extra effective

Warnings

• For external use only.
• Do not use on broken skin .
• Ask a doctor before use if you have kidney disease.
• Stop use if rash or irritation occurs.

• Keep out of reach of children.

If swallowed, get medical help or contact a Poison Control Center right away.

Directions

• apply to underarms only
• before bed, apply two clicks of product to each underarm

Other information

Do not store over 115°F

Inactive ingredients

Cyclopentasiloxane, Dimethicone, Microcrystalline Wax, Paraffin, Fragrance (Parfum), Silica, Dimethicone Crosspolymer, Helianthus Annuus (Sunflower) Seed Oil, BHT, Benzyl Alcohol, Benzyl Salicylate, Cinnamyl Alcohol, Citronellol, Eugenol, Geraniol, Hexyl Cinnamal, Isoeugenol, Linalool

Questions?

Call toll-free 1-800-761-3683